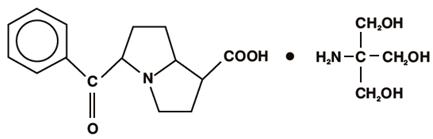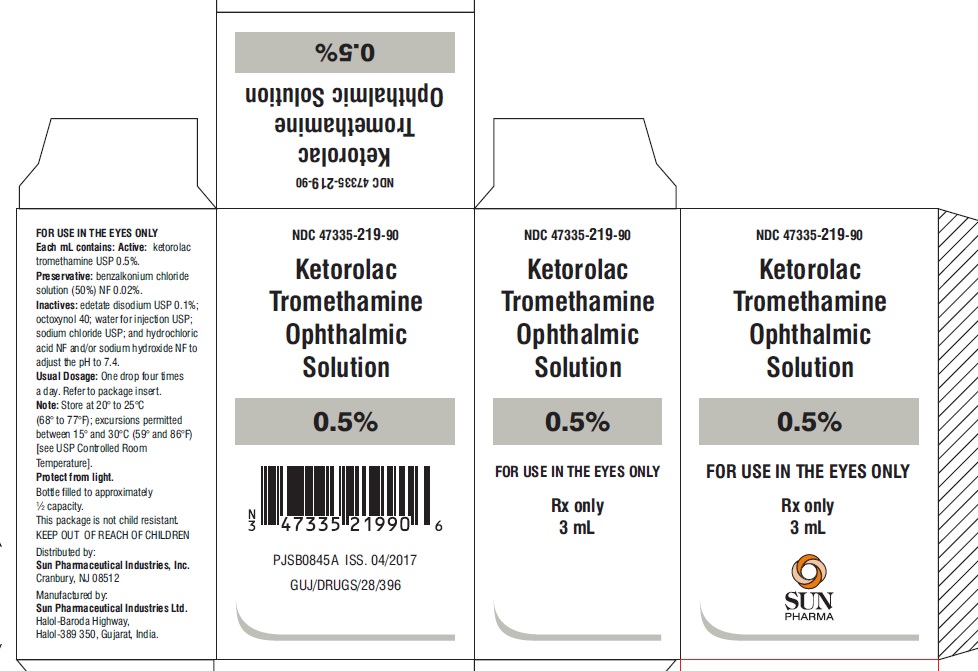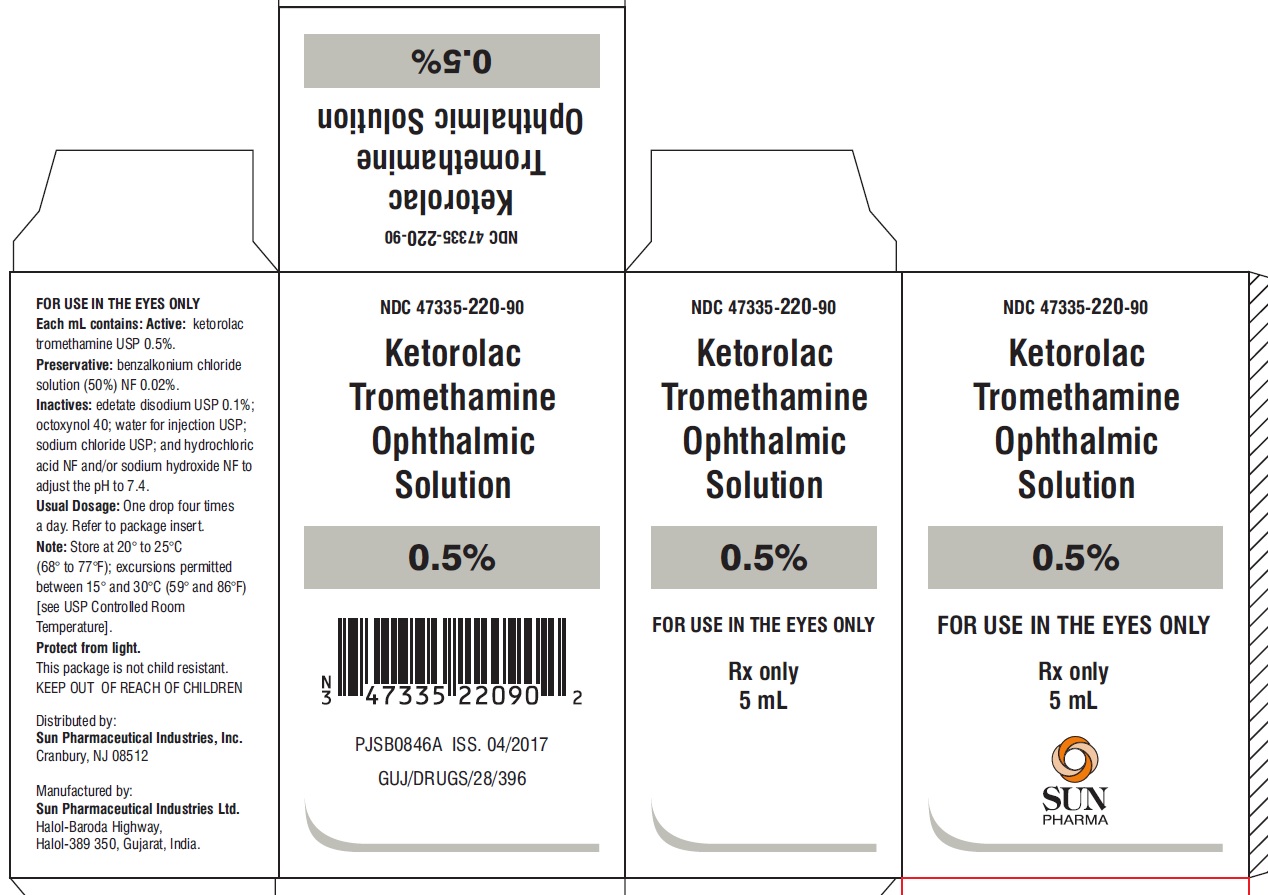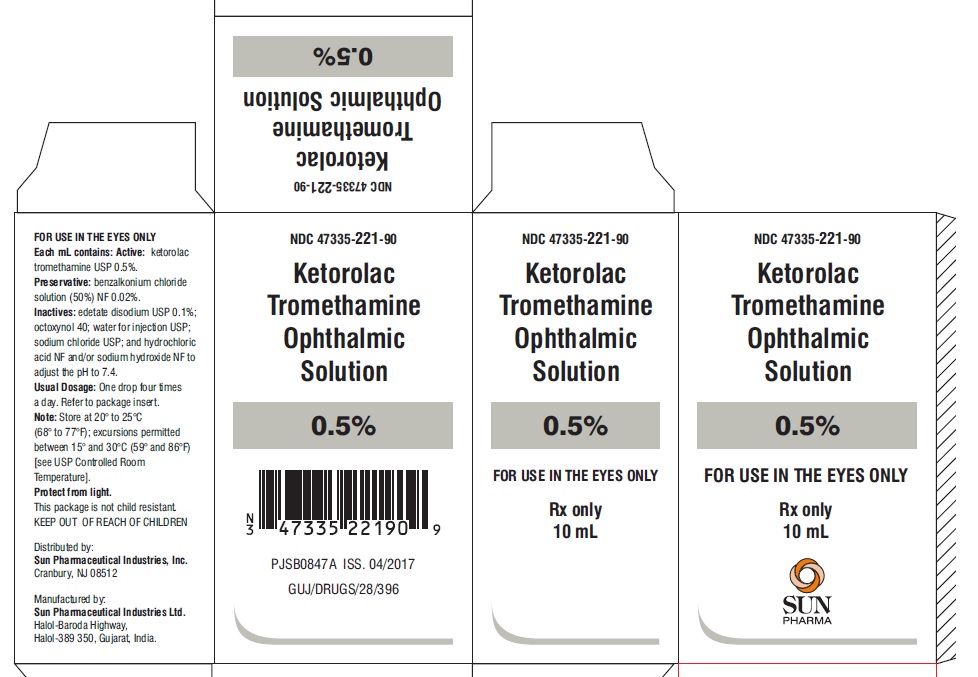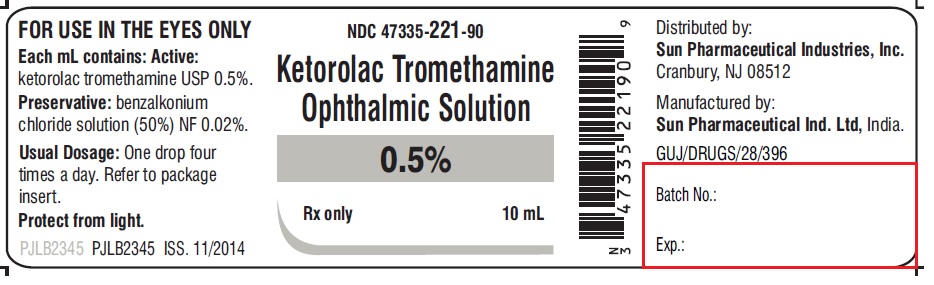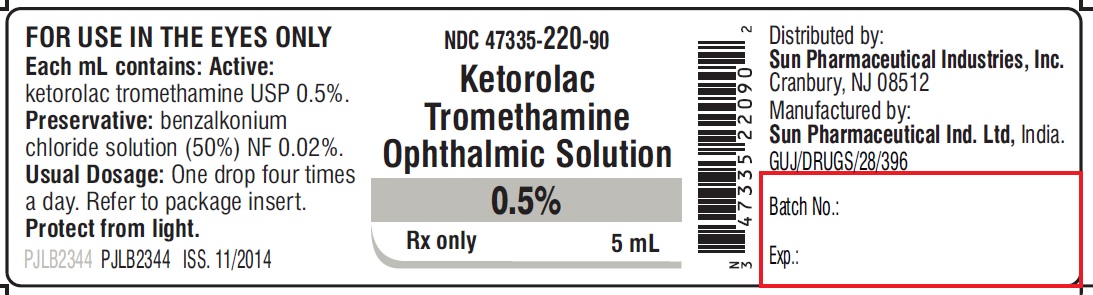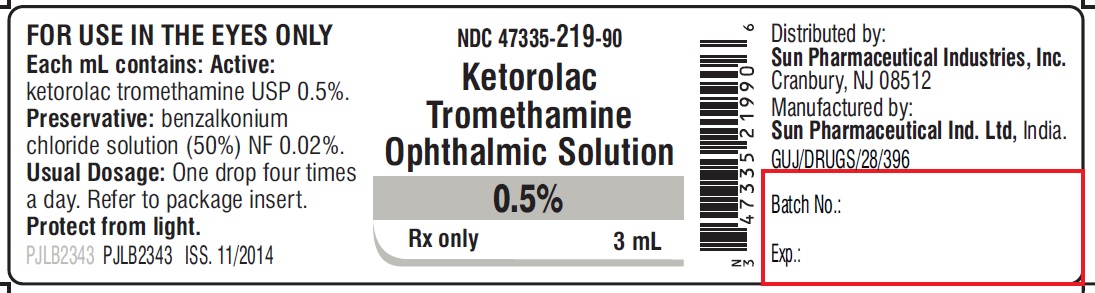 DRUG LABEL: Ketorolac Tromethamine
NDC: 47335-219 | Form: SOLUTION/ DROPS
Manufacturer: Sun Pharmaceutical Industries, Inc.
Category: prescription | Type: Human Prescription Drug Label
Date: 20181024

ACTIVE INGREDIENTS: KETOROLAC TROMETHAMINE 5 mg/1 mL
INACTIVE INGREDIENTS: BENZALKONIUM CHLORIDE; EDETATE DISODIUM; OCTOXYNOL-40; SODIUM CHLORIDE; HYDROCHLORIC ACID; SODIUM HYDROXIDE; WATER

HIGHLIGHTS OF PRESCRIBING INFORMATION

These highlights do not include all the information needed to use KETOROLAC TROMETHAMINE ophthalmic solution safely and effectively. See full prescribing information for KETOROLAC TROMETHAMINE ophthalmic solution.
KETOROLAC TROMETHAMINE ophthalmic solution 0.5%
Initial U.S. Approval: 1991

1 INDICATIONS AND USAGE

Ketorolac tromethamine ophthalmic solution is a nonsteroidal, anti-inflammatory indicated for:

- The treatment of inflammation following cataract surgery. (1)
- The temporary relief of ocular itching due to seasonal allergic conjunctivitis. (1)

2 DOSAGE AND ADMINISTRATION

One drop of ketorolac tromethamine ophthalmic solution should be applied to the affected eye(s) four times a day for relief of ocular itching due to seasonal allergic conjunctivitis.
For the treatment of postoperative inflammation in patients who have undergone cataract extraction, one drop of ketorolac tromethamine ophthalmic solution should be applied to the affected eye four times daily beginning 24 hours after cataract surgery and continuing through the first 2 weeks of the postoperative period. (2.1)

3 DOSAGE FORMS AND STRENGTHS

Ophthalmic solution containing 5 mg/mL ketorolac tromethamine. (3)

- 5 mL size bottle filled with 3 mL of solution
- 5 mL size bottle filled with 5 mL of solution
- 10 mL size bottle filled with 10 mL of solution

4 CONTRAINDICATIONS

Hypersensitivity to any component of this product. (4)

5 WARNINGS AND PRECAUTIONS

- Delayed healing (5.1)
- Cross-sensitivity or hypersensitivity (5.2)
- Increased bleeding time due to interference with thrombocyte aggregation (5.3)
- Corneal effects including keratitis (5.4)

6 ADVERSE REACTIONS

The most frequent adverse reactions reported by up to 40% of patients participating in clinical trials have been transient stinging and burning on instillation. (6.1)
To report SUSPECTED ADVERSE REACTIONS, contact Sun Pharmaceutical Industries, Inc. at 1-800-818-4555 or FDA at 1-800-FDA-1088 or www.fda.gov/medwatch.

FULL PRESCRIBING INFORMATION

1 INDICATIONS AND USAGE

Ketorolac tromethamine ophthalmic solution is indicated for the temporary relief of ocular itching due to seasonal allergic conjunctivitis. Ketorolac tromethamine ophthalmic solution is also indicated for the treatment of postoperative inflammation in patients who have undergone cataract extraction.

2 DOSAGE AND ADMINISTRATION

2.1 Recommended Dosing

Patient Dosing
The recommended dose of ketorolac tromethamine ophthalmic solution is one drop four times a day to the affected eye(s) for relief of ocular itching due to seasonal allergic conjunctivitis.
For the treatment of postoperative inflammation in patients who have undergone cataract extraction, one drop of ketorolac tromethamine ophthalmic solution should be applied to the affected eye four times daily beginning 24 hours after cataract surgery and continuing through the first 2 weeks of the postoperative period.

2.2 Use with Other Topical Ophthalmic Medications

Ketorolac tromethamine ophthalmic solution has been safely administered in conjunction with other ophthalmic medications such as antibiotics, alpha-agonists, beta blockers, carbonic anhydrase inhibitors, cycloplegics, and mydriatics. Drops should be administered at least 5 minutes apart.

3 DOSAGE FORMS AND STRENGTHS

Ketorolac tromethamine ophthalmic solution 0.5% is supplied sterile in white opaque LDPE dropper bottles with white opaque plug and sealed with gray pantone opaque pilfer-proof caps as follows:

- 5 mL size bottle filled with 3 mL of solution
- 5 mL size bottle filled with 5 mL of solution
- 10 mL size bottle filled with 10 mL of solution

4 CONTRAINDICATIONS

Ketorolac tromethamine ophthalmic solution is contraindicated in patients with previously demonstrated hypersensitivity to any of the ingredients in the formulation.

5 WARNINGS AND PRECAUTIONS

5.1 Delayed Healing

Topical nonsteroidal anti-inflammatory drugs (NSAIDs) may slow or delay healing. Topical corticosteroids are also known to slow or delay healing. Concomitant use of topical NSAIDs and topical steroids may increase the potential for healing problems.

5.2 Cross-Sensitivity or Hypersensitivity

There is the potential for cross-sensitivity to acetylsalicylic acid, phenylacetic acid derivatives, and other NSAIDs. There have been reports of bronchospasm or exacerbation of asthma associated with the use of ketorolac tromethamine ophthalmic solution in patients who have either a known hypersensitivity to aspirin/non-steroidal anti-inflammatory drugs or a past medical history of asthma. Therefore, caution should be used when treating individuals who have previously exhibited sensitivities to these drugs.

5.3 Increased Bleeding Time

With some NSAIDs, there exists the potential for increased bleeding time due to interference with thrombocyte aggregation. There have been reports that ocularly applied nonsteroidal anti- inflammatory drugs may cause increased bleeding of ocular tissues (including hyphemas) in conjunction with ocular surgery.
It is recommended that ketorolac tromethamine ophthalmic solution be used with caution in patients with known bleeding tendencies or who are receiving other medications, which may prolong bleeding time.

5.4 Corneal Effects

Use of topical NSAIDs may result in keratitis. In some susceptible patients, continued use of topical NSAIDs may result in epithelial breakdown, corneal thinning, corneal erosion, corneal ulceration, or corneal perforation. These events may be sight threatening. Patients with evidence of corneal epithelial breakdown should immediately discontinue use of topical NSAIDs and should be closely monitored for corneal health.
Postmarketing experience with topical NSAIDs suggests that patients with complicated ocular surgeries, corneal denervation, corneal epithelial defects, diabetes mellitus, ocular surface diseases (e.g., dry eye syndrome), rheumatoid arthritis, or repeat ocular surgeries within a short period of time may be at increased risk for corneal adverse events which may become sight threatening. Topical NSAIDs should be used with caution in these patients.
Postmarketing experience with topical NSAIDs also suggests that use more than 1 day prior to surgery or use beyond 14 days post-surgery may increase patient risk for the occurrence and severity of corneal adverse events.

5.5 Contact Lens Wear

Ketorolac tromethamine ophthalmic solution should not be administered while wearing contact lenses.

6 ADVERSE REACTIONS

6.1 Clinical Studies Experience

Because cli nical studies are conducted under wi dely var ying conditions, adverse reaction rates observed in the clinical studies of a drug cannot be directly compared to t he rates in the clinical studies of another drug and may not reflect t he rates observed in practice.

The most fr equent adverse react ions reported with the use of k etorolac tro meth a mine ophthal mic solutio ns have been tra nsient stin gi ng and burni ng on instillation. These reactions were reported by up to 40% of patie nts partici pating in clinic al t rials.

Other adverse reactions occurring approxi mately 1 to 10% of the ti me during tre at ment with ketor olac tr ometh a mine ophthal mic solutio ns inc luded aller gic reactions, corneal ede ma, iritis, ocular inflammation, ocular ir rit ati on, super fici al ker atitis, and super ficial ocular in fectio ns.

Other adverse reactions reported rarely with the use of ketorolac tro metha mine ophthal mic solutio ns included: c orneal infiltrates, corneal ulcer, eye dry ness, headac hes, and visual disturbance (blurry vision).

6.2 Postmarketing Experience

The following adverse reactions have been identified during postmarketing use of ketorolac tromethamine ophthalmic solution 0.5% in clinical practice. Because they are reported voluntarily from a population of unknown size, estimates of frequency cannot be made. The reactions, which have been chosen for inclusion due to either their seriousness, frequency of reporting, possible causal connection to topical ketorolac tromethamine ophthalmic solution 0.5% or a combination of these factors, include bronchospasm or exacerbation of asthma, corneal erosion, corneal perforation, corneal thinning, and epithelial breakdown [see Warnings and Precautions (5.2, 5.4)].

8 USE IN SPECIFIC POPULATIONS

8.1 Pregnancy

Teratogenic Effects. P regnancy Category C

Pregnancy Category C: Ketorolac tr o metha min e, ad ministered during organogenesis, was not teratogenic in rabbits and rats at oral doses of 3.6 mg/kg/day and 10 mg/ kg/day, respectively. These doses are approxi mately 100 ti mes and 250 ti mes higher respectively than the max i m um recom mended hu man topical op hthal mic daily d ose of 2 mg (5 mg / mL x 0.05 mL/drop, x 4 drops x 2 eyes) to affected eyes on a mg/kg basis. Additionally, when ad ministered to rats after Day 17 of gestation at oral doses up to 1.5 mg/ k g/day (approxi mately 40 ti mes the typical hu man topical ophthal mic daily dose), ketorolac tro me tha mine resulted in dystocia and increased pup mortality. There are no adequate a nd well-controlled studies in pregnant w o men. Keto ro lac t ro met ham ine op htha lm ic so lut i on should be used during pregnancy only if the potential bene fit j usti fies the p otential risk to the fetus.

Nonterato genic Effect s: Because of the known effects of prostaglandin-inhibiting drugs on the fetal c ardio vascul ar syst em (closure of the ductus art eriosu s), the use of keto ro lac t ro met ham ine op htha lm ic so lut i on during late pregnancy should be avoided.

8.3 Nursing Mothers

Because many drugs are excreted in human milk, caution should be exercised when ketorolac tromethamine ophthalmic solution is administered to a nursing woman.

8.4 Pediatric Use

Safety and efficacy in pediatric patients bel ow t he age of 2 have not been esta blished.

8.5 Geriatric Use

No overall clinical di fferences in sa fety or effectiveness have been observed between elderly and other ad ult patie nts.

11 DESCRIPTION

Keto ro lac t ro met ham ine op htha lm ic so lut i on 0.5% is a m ember of the pyrrolo-pyrrole group of nonsteroidal anti-inflammatory drugs (NSAIDs) for ophthal mic use. Its che mical na me is (±)-5-Benzoyl-2, 3-dihydro-1H pyrrolizi ne-1-carboxylic acid co m pound with 2-a mino-2-(hydroxy methyl)-1,3-propanediol (1:1) and it has the following structure:

Keto ro lac t ro met ham ine op htha lm ic so lut i on is supplied as a sterile isotonic aqueous 0.5% solution, with a pH of 7.4. Keto ro lac t ro met ham ine op htha lm ic so lut i on is a race mic m ixture of R-(+) and S-(-)- ketor olac tro metha mine. Ketorol ac tro methamine may exist in t hree cr ystal for ms. All for ms are equally soluble in water. The pKa of ketorolac is 3.5. This white to o ff-white c rystalline su bstance discolors on prolonged exposure to light. The m o lecular weight of ketorolac tro metha mine is 376.41. The os molality of keto ro lac t ro met ham ine op htha lm ic so lut i on is 290 m O s mol/kg.

Each mL of ketorolac tromethamine ophthalmic solution contains: Active: ketorolac tromethamine USP 0.5%. Preservative: benzalkonium chloride solution (50%) NF 0.02%. Inactives: edetate disodium USP 0.1%; octoxynol 40; water for injection USP; sodium chloride USP; hydrochloric acid NF and/or sodium hydroxide NF to adjust the pH.

12 CLINICAL PHARMACOLOGY

12.1 Mechanism of Action

Ketorolac tr o metha mine is a nonsteroidal ant i-inflammatory drug which, when a d ministered syste micall y, has de monstrated anal gesic, a nti-inflam matory, and anti-pyretic activity. The mechani sm of its action is thought to be due to i ts ability to inhibit prostaglandin biosynthesis.

12.3 Pharmacokinetics

Two drops of 0.5% ketorolac tro metha mine ophthal mic solution instilled into the eyes of patients 12 hours and 1 hour prior to cataract extraction achieved a mean ketorolac concentration of 95 ng/ mL in the aqueous h u mor of 8 of 9 eyes tested (range 40 to 170 ng/mL).

One drop of 0.5% ketorolac tro metha mine ophthal mic solution was instilled into 1 eye and 1 drop of vehicle into the other eye TID in 26 healthy subjects. Five (5) of 26 subjects had dete ctable concent ratio ns of ketorol ac in th eir plas ma (range 11 to 23 ng/mL) at Day 10 during topical ocular treat ment. The range of concent rations following TID dosing of 0.5% ketorolac tro metha mi ne ophthal mic solution are approxi mately 4 to 8% of the steady state mean min i m um plas ma concentration observed following four ti mes daily oral a d ministration of 10 mg ketorolac in hu mans (290 ± 70 ng/mL).

13 NONCLINICAL TOXICOLOGY

13.1 Carcinogenesis, Mutagenesis,Impairment of Fertility

Ketorolac tr o metha mine was not ca rcinogenic in either rats given up to 5 mg/kg/day orally for 24 months or in mice given 2 mg /kg/day orally for 18 months. These doses are approximately 125 ti mes and 50 ti mes higher respectively than the maxi m um re com mended h u man topical ophthal mic daily dose given as QID for itching to affected eyes on a mg/kg basis.

Ketorolac tromethamine was not mutagenic in vitro in the Ames assay or in forward mutation assays. Si milarly, it did not result in an in vitro increase in unscheduled DNA synthesis or an in vivo i ncrea se in chro moso me breakage in mice. However, ketorolac trometha mine did result in an increased incide nce in chro mosomal ab err atio ns in Chinese ha mster ovary cells.

Ketorol ac t ro metha mine did not i mpair fe rtility when ad ministered orally to male and fe male rats at doses up to 9 mg/kg/day and 16 mg/kg/day, respectively. These doses are respectively 225 and 400 ti mes higher than the typical h u man topical ophthal mic daily dose.

14 CLINICAL STUDIES

Two controlled clinical studies sho wed that k etorolac tro metha mine ophthal mic solution was significa ntly more effective than its vehicle in relieving ocular itching caused by seasonal all ergic conjuncti vitis.

Two controlled clinical studies sho wed that pati ents t reated for two weeks with ket o rolac tro metha mi ne ophthal mic solution were less likely to have measurable signs of inflammation (cell and flare) than patients treated with its ve hicle.

Results from clinical studies indicate that k etorolac tro metha mine has no significant effect upon intraocular pressure; ho wever, chan ges in intraoc ular pressure may occur following cataract surgery.

16 HOW SUPPLIED/STORAGE AND HANDLING

Ketorolac tromethamine ophthalmic solution 0.5% is supplied sterile in white opaque LDPE dropper bottles with white opaque plug and sealed with gray pantone opaque pilfer-proof caps as follows:

3 mL in 5 mL bottle NDC 47335-219-90

5 mL in 5 mL bottle NDC 47335-220-90

10 mL in 10 mL bottle NDC 47335-221-90

Store at 20° to 25°C (68° to 77°F); excursions permitted between 15° and 30°C (59° and 86°F) [see USP Controlled Room Temperature]. Protect from light.

17 PATIENT COUNSELING INFORMATION

17.1 Slow or Delayed Healing

Patie nts sh ould be in fo r med of the possibility that slow or delayed healing may occur while using nonsteroidal anti-inflammatory drugs (NSAIDs).

17.2 Avoiding Contamination of the Product

Patie nts sh ould be in str ucted to avoid allow ing the tip of the bottle to co ntact the eye or surrounding structures because this could cause the tip to beco me cont a m inated by common bacteria kn own to cause ocular infections. Serious da mage to the eye and subsequent loss of vision may result from using contaminated solutions.

Also, to avoid the potential for cross-conta mina tion, the patient should be advised to use one bottle for e ach eye foll owing bil ate ral ocular s u rgery. The use of the s a me bottle of topic al eye drops for both eyes following bilateral ocular surgery is not recom mend ed.

17.3 Contact Lens Wear

Patients should be advised that keto ro lac t ro met ham ine op htha lm ic so lut i on should not be ad ministered while wearing contact lenses.

17.4 Intercurrent Ocular Conditions

Patients should be advised that if they develop an intercurrent ocular condition (e.g., trau ma or infection) or have ocular surgery, they should i mmediately seek their physician’s advice concerning the continued use of keto ro lac t ro met ham ine op htha lm ic so lut i on.

17.5 Concomitant Topical Ocular Therapy

Patie nts sh ould be advi sed that if m ore than one topical op ht hal mic medication is being used, the medicines should be ad ministered at least 5 minutes apart.
Distributed by:
Sun Pharmaceutical Industries, Inc.
Cranbury, NJ 08512
PJPI0496A
ISS. 07/2017

PACKAGE LABEL.PRINCIPAL DISPLAY PANEL -label-3 mL

NDC 47335-219-90
Ketorolac Tromethamine Ophthalmic Solution
0.5%
Rx only
3 mL

PACKAGE LABEL.PRINCIPAL DISPLAY PANEL -Carton- 3 mL

NDC 47335-219-90
Ketorolac Tromethamine Ophthalmic Solution
0.5%
FOR USE IN THE EYES ONLY
Rx only
3 mL
SUN PHARMA

PACKAGE LABEL.PRINCIPAL DISPLAY PANEL -Label -5 mL

NDC 47335-220-90
Ketorolac Tromethamine Ophthalmic Solution
0.5%
Rx only
5mL

PACKAGE LABEL.PRINCIPAL DISPLAY PANEL -Carton -5 mL

NDC 47335-220-90
Ketorolac Tromethamine Ophthalmic Solution
0.5%
FOR USE IN THE EYES ONLY
Rx only
5 mL
SUN PHARMA

PACKAGE LABEL.PRINCIPAL DISPLAY PANEL - Label -10 mL

NDC 47335-221-90
Ketorolac Tromethamine Ophthalmic Solution
0.5%
Rx only
10 mL

PACKAGE LABEL.PRINCIPAL DISPLAY PANEL -Carton -10 mL

NDC 47335-221-90
Ketorolac Tromethamine Ophthalmic Solution
0.5%
FOR USE IN THE EYES ONLY
Rx only
10 mL
SUN PHARMA